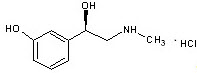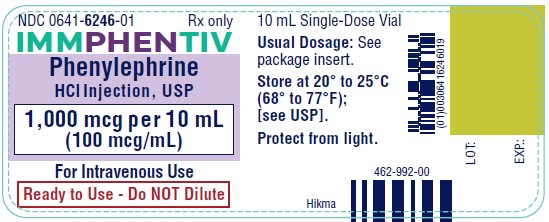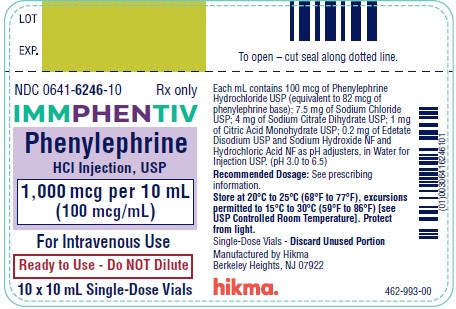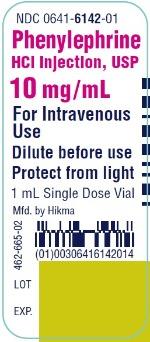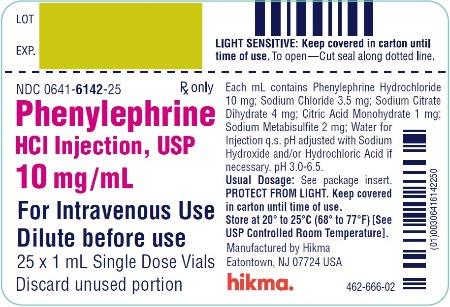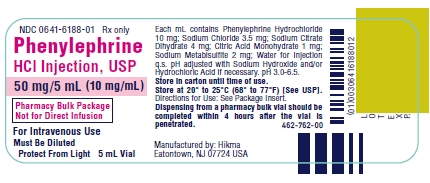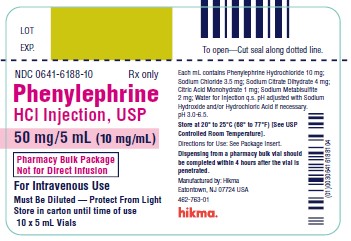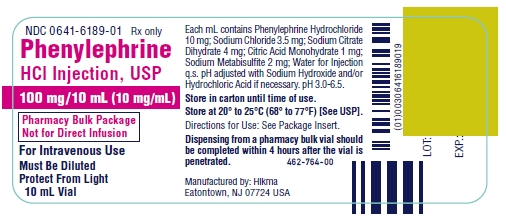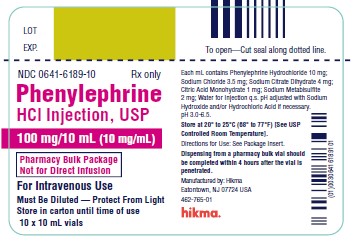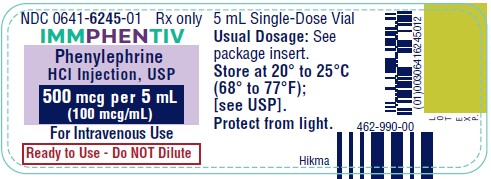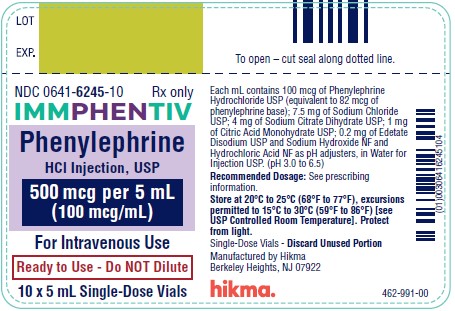 DRUG LABEL: Phenylephrine Hydrochloride
NDC: 0641-6142 | Form: INJECTION
Manufacturer: Hikma Pharmaceuticals USA Inc.
Category: prescription | Type: HUMAN PRESCRIPTION DRUG LABEL
Date: 20240409

ACTIVE INGREDIENTS: PHENYLEPHRINE HYDROCHLORIDE 10 mg/1 mL
INACTIVE INGREDIENTS: SODIUM CHLORIDE 3.5 mg/1 mL; CITRIC ACID MONOHYDRATE 1 mg/1 mL; TRISODIUM CITRATE DIHYDRATE 4 mg/1 mL; WATER; SODIUM METABISULFITE 2 mg/1 mL; SODIUM HYDROXIDE; HYDROCHLORIC ACID

HIGHLIGHTS OF PRESCRIBING INFORMATION

These highlights do not include all the information needed to use IMMPHENTIV® and PHENYLEPHRINE HYDROCHLORIDE safely andeffectively. See full prescribing information for IMMPHENTIV® and PHENYLEPHRINE HYDROCHLORIDE.
IMMPHENTIV® (phenylephrine hydrochloride) injection for intravenous bolus use only
PHENYLEPHRINE HYDROCHLORIDE injection, for intravenous use
Initial U.S. Approval: 2012

RECENT MAJOR CHANGES

Indications and Usage (1)............................................................ 03/2023

Dosage and Administration (2.1, 2.2)........................................... 03/2023

1 INDICATIONS AND USAGE

IMMPHENTIV injection 100 mcg/mL is an alpha-1 adrenergic receptor agonist indicated for increasing blood pressure in adults with clinically important hypotension resulting primarily from vasodilation in the setting of anesthesia.

Phenylephrine Hydrochloride Injection 10 mg/mL is alpha-1 adrenergic receptor agonist indicated for increasing blood pressure in adults with clinically important hypotension resulting primarily from vasodilation in the settings of anesthesia and septic shock.

2 DOSAGE AND ADMINISTRATION

IMMPHENTIV Injection 100 mcg/mL:

- Do NOT dilute prior to administration (2.1)

Dosing for Perioperative Hypotension

- Intravenous bolus administration: 50 mcg to 250 mcg (2.2)

Phenylephrine Hydrochloride Injection 10 mg/mL:

- MUST BE DILUTED before administration. (2.1)
  Dosing for Perioperative Hypotension
  - Intravenous bolus administration: 50 mcg to 250 mcg (2.2)
  - Intravenous continuous infusion: 0.5 mcg/kg/minute to 1.4 mcg/kg/minute titrated to effect (2.2)
  Dosing for Patients with Vasodilatory Shock
  - Intravenous continuous infusion: 0.5 mcg/kg/minute to 6 mcg/kg/minute titrated to effect (2.2)

3 DOSAGE FORMS AND STRENGTHS

IMMPHENTIV® Injection:

- 500 mcg in 5 mL (100 mcg/mL) of Phenylephrine hydrochloride in a single-dose Ready-To-Use vial (3)
- 1,000 mcg in 10 mL (100 mcg/mL) of Phenylephrine hydrochloride in a single-dose Ready-To-Use vial (3)

Phenylephrine Hydrochloride Injection:

- 10 mg in 1 mL (10 mg/mL) of Phenylephrine hydrochloride in a single-dose vial (3)
- 50 mg in 5 mL (10 mg/mL) of Phenylephrine hydrochloride in a pharmacy bulk package vial (3)
- 100 mg in 10 mL (10 mg/mL) of Phenylephrine hydrochloride in a pharmacy bulk package vial (3)

4 CONTRAINDICATIONS

- Hypersensitivity to the products or any of their components (4)

5 WARNINGS AND PRECAUTIONS

- Severe bradycardia and decreased cardiac output: (5.2)
- Extravasation: during intravenous administration may cause necrosis or sloughing of tissue (5.4)
- Concomitant use with oxytocic drugs: pressor effect of sympathomimetic pressor amines is potentiated (5.5)
- Allergic-type reactions with Phenylephrine Hydrochloride Injection 10 mg/mL: Sulfite (5.6)

6 ADVERSE REACTIONS

Most common adverse reactions: nausea and vomiting, headache, nervousness (6)

To report SUSPECTED ADVERSE REACTIONS, contact Hikma Pharmaceuticals USA Inc. at 1-877-845-0689 or FDA at 1-800-FDA-1088 or www.fda.gov/medwatch.

7 DRUG INTERACTIONS

- Agonistic effects with monoamine oxidase inhibitors (MAOI), β-adrenergic blocking agents, α-2 adrenergic agonists, steroids, tricyclic antidepressants, norepinephrine transport inhibitors, ergot alkaloids, centrally-acting sympatholytic agents and atropine sulfate (7.1)
- Antagonistic effects on and by α-adrenergic blocking agents (7.2)

FULL PRESCRIBING INFORMATION

1 INDICATIONS AND USAGE

IMMPHENTIV injection 100 mcg/mL is indicated for increasing blood pressure in adults with clinically important hypotension resulting primarily from vasodilation in the setting of anesthesia.

Phenylephrine Hydrochloride Injection 10 mg/mL is indicated for increasing blood pressure in adults with clinically important hypotension resulting primarily from vasodilation in the settings of anesthesia and septic shock.

2 DOSAGE AND ADMINISTRATION

2.1 General Administration Instructions

Phenylephrine Hydrochloride Injection is injected by bolus intravenous infusion or in dilute solution as a continuous intravenous infusion.

2.2 Preparation of Phenylephrine Hydrochloride Injection

Preparing a 100 mcg/mL Solution for Intravenous Bolus Administration

For intravenous bolus administration, withdraw 10 mg (1 mL of a 10 mg/mL concentration) of Phenylephrine Hydrochloride Injection 10 mg/mL and dilute with 99 mL of 5% Dextrose Injection, USP or 0.9% Sodium Chloride Injection, USP. This will yield a final concentration of 100 mcg/mL. Withdraw an appropriate dose from the 100 mcg/mL solution prior to intravenous bolus administration.

Preparing a 20 mcg/mL Solution for Continuous Intravenous Infusion

For continuous intravenous infusion, withdraw 10 mg (1 mL of 10 mg/mL concentration) of phenylephrine hydrochloride injection 10 mg/mL and add to 500 mL of 5% Dextrose Injection, USP or 0.9% Sodium Chloride Injection, USP (providing a final concentration of 20 mcg/mL).

Directions for Dispensing from Phenylephrine Hydrochloride Injection 10 mg/mL Pharmacy Bulk Vial

The Pharmacy Bulk Vial is intended for dispensing of single doses to multiple patients in a pharmacy admixture program and is restricted to the preparation of admixtures for infusion. Each closure shall be penetrated only one time with a suitable sterile transfer device or dispensing set that allows measured dispensing of the contents. The Pharmacy Bulk Vial is to be used only in a suitable work area such as a laminar flow hood (or an equivalent clean air compounding area). Dispensing from a pharmacy bulk vial should be completed within 4 hours after the vial is penetrated.

Dosing for Perioperative Setting

In adult patients undergoing surgical procedures with either neuraxial anesthesia or general anesthesia:

- IMMPHENTIV Injection 100 mcg/mL and Phenylephrine Hydrochloride Injection 10 mg/mL (diluted to 100 mcg/mL): 50 mcg to 250 mcg by intravenous bolus administration. The most frequently reported initial bolus dose is 50 mcg or 100 mcg.
- Phenylephrine Hydrochloride Injection 10 mg/mL (diluted to 20 mcg/mL): 0.5 mcg/kg/min to 1.4 mcg/kg/min by intravenous continuous infusion, titrated to blood pressure goal.

Dosing for Septic or Other Vasodilatory Shock (Phenylephrine Hydrochloride Injection 10 mg/mL only)

In adult patients with septic or other vasodilatory shock:

- No bolus.
- 0.5 mcg/kg/min to 6 mcg/kg/min by intravenous continuous infusion, titrated to blood pressure goal. Doses above 6 mcg/kg/min do not show significant incremental increase in blood pressure.

3 DOSAGE FORMS AND STRENGTHS

IMMPHENTIV® injection, USP: 100 mcg/mL phenylephrine hydrochloride is a clear, colorless, essentially free of visible foreign matter sterile parenteral solution, available in two vial sizes:

- 500 mcg in 5 mL (100 mcg/mL) of Phenylephrine hydrochloride in a single-dose Ready-To-Use vial
- 1,000 mcg in 10 mL (100 mcg/mL) of Phenylephrine hydrochloride in a single-dose Ready-To-Use vial

Phenylephrine Hydrochloride Injection, USP: 10 mg/mL phenylephrine hydrochloride is a clear, colorless, essentially free of visible foreign matter sterile parenteral solution, available in three vial sizes:

- 10 mg in 1 mL (10 mg/mL) of Phenylephrine hydrochloride in a single-dose vial
- 50 mg in 5 mL (10 mg/mL) of Phenylephrine hydrochloride in a pharmacy bulk package vial
- 100 mg in 10 mL (10 mg/mL) of Phenylephrine hydrochloride in a pharmacy bulk package vial

4 CONTRAINDICATIONS

The use of IMMPHENTIV 100 mcg/mL and Phenylephrine Hydrochloride Injection 10 mg/mL is contraindicated in patients with:

- Hypersensitivity to the products or any of their components

5 WARNINGS AND PRECAUTIONS

5.1 Exacerbation of Angina, Heart Failure, or Pulmonary Arterial Hypertension

Because of its pressor effects, phenylephrine hydrochloride can precipitate angina in patients with severe arteriosclerosis or history of angina, exacerbate underlying heart failure, and increase pulmonary arterial pressure.

5.2 Bradycardia

IMMPHENTIV 100 mcg/mL and Phenylephrine Hydrochloride Injection 10 mg/mL can cause severe bradycardia and decreased cardiac output.

5.3 Risk in Patients with Autonomic Dysfunction

The pressor response to adrenergic drugs, including phenylephrine, can be increased in patients with autonomic dysfunction, as may occur with spinal cord injuries.

5.4 Skin and Subcutaneous Necrosis

Extravasation of phenylephrine can cause necrosis or sloughing of tissue.

5.5 Pressor Effect with Concomitant Oxytocic Drugs

Oxytocic drugs potentiate the pressor effect of sympathomimetic pressor amines including IMMPHENTIV 100 mcg/mL and Phenylephrine Hydrochloride Injection 10 mg/mL [see Drug Interactions (7.1)], with the potential for hemorrhagic stroke.

5.6 Allergic Reactions

Phenylephrine Hydrochloride Injection 10 mg/mL contains sodium metabisulfite, a sulfite that may cause allergic-type reactions, including anaphylactic symptoms and life-threatening or less severe asthmatic episodes in certain susceptible people. The overall prevalence of sulfite sensitivity in the general population is unknown and probably low. Sulfite sensitivity is seen more frequently in asthmatic than in nonasthmatic people.

5.7 Peripheral and Visceral Ischemia

IMMPHENTIV 100 mcg/mL and Phenylephrine Hydrochloride Injection 10 mg/mL can cause excessive peripheral and visceral vasoconstriction and ischemia to vital organs, particularly in patients with extensive peripheral vascular disease.

5.8 Renal Toxicity

IMMPHENTIV 100 mcg/mL and Phenylephrine Hydrochloride Injection 10 mg/mL can increase the need for renal replacement therapy in patients with septic shock. Monitor renal function.

6 ADVERSE REACTIONS

The following adverse reactions associated with the use of phenylephrine hydrochloride were identified in the literature. Because these reactions are reported voluntarily from a population of uncertain size, it is not always possible to estimate their frequency reliably or to establish a causal relationship to drug exposure.

Cardiac disorders: Bradycardia, AV block, ventricular extrasystoles, myocardial ischemia

Gastrointestinal disorders: Nausea, vomiting

General disorders and administrative site conditions: Chest pain, extravasation

Immune system disorders: Sulfite sensitivity

Nervous system disorders: Headache, nervousness, paresthesia, tremor

Psychiatric disorders: Excitability

Respiratory: Pulmonary edema, rales

Skin and subcutaneous tissue disorders: Diaphoresis, pallor, piloerection, skin blanching, skin necrosis with extravasation

Vascular disorders: Hypertensive crisis

7 DRUG INTERACTIONS

7.1 Agonists

The pressor effect of phenylephrine hydrochloride is increased in patients receiving:

- Monoamine oxidase inhibitors (MAOI), such as selegiline.
- β-adrenergic blockers
- α-2 adrenergic agonists, such as clonidine
- Steroids
- Tricyclic antidepressants
- Norepinephrine transport inhibitors, such as atomoxetine
- Ergot alkaloids, such as methylergonovine maleate
- Centrally-acting sympatholytic agents, such as guanfacine or reserpine
- Atropine sulfate

7.2 Antagonists

α-adrenergic blocking agents, including phenothiazines (e.g., chlorpromazine) and amiodarone block phenylephrine and are in turn blocked by phenylephrine.

8 USE IN SPECIFIC POPULATIONS

8.1 Pregnancy

Risk Summary

In animal reproductive and developmental studies, decreased fetal body weights were noted at 0.4 times the human daily dose (HDD) of 10 mg. No malformations were reported, however, an increased incidence of agenesis of the intermediate lobe of the lung, a visceral variation, was reported at levels as low as 0.08 times the HDD.

The estimated background risk of major birth defects and miscarriage for the indicated population is unknown. All pregnancies have a background risk of birth defect, loss, or other adverse outcomes. In the U.S. general population, the estimated background risk of major birth defects and miscarriage in clinically recognized pregnancies is 2 to 4% and 15 to 20%, respectively.

Data

Animal Data

No malformations were noted when normotensive pregnant rats were treated with a single daily intravenous bolus dose of 50 mcg, 150 mcg, or 300/200 mcg/kg phenylephrine hydrochloride from Gestation Day 6 to 17 (high dose is 0.3/0.2 times the human daily dose (HDD) of 10 mg/day based on body surface area). Evidence of maternal toxicity, including mortality, was noted at the highest tested dose of 300/200 mcg/kg.

Decreased fetal body weights but no clear treatment-related malformations were reported when normotensive pregnant rabbits were treated with a single daily intravenous bolus dose of 40 mcg, 100 mcg and 200 mcg/kg (0.08, 0.2, and 0.4 times the HDD based on body surface area) phenylephrine hydrochloride from Gestation Day 7 to 19. Maternal toxicity, as manifested by decreased food consumption and body weight gain at all doses. An increased incidence of agenesis of the intermediate lobe of the lung, a visceral variation, was noted in all treatment groups compared to controls.

No adverse effects on the offspring were reported when pregnant rats were treated via a single daily intravenous bolus dose of up to 200 mcg/day phenylephrine hydrochloride (0.2 times the HDD based on body surface area) from Gestation Day 6 to Lactation Day 20.

Pregnancy Category B

Animal reproduction studies have not been conducted with phenylephrine. It is also not known whether phenylephrine can cause fetal harm when administered to a pregnant woman or can affect reproduction capacity. Phenylephrine should be given to a pregnant woman only if clearly needed. However, the safety of its use for the management of hypotension associated with neuraxial anesthesia in cesarean deliveries is well established.^71

8.4 Pediatric Use

Safety and effectiveness in pediatric patients have not been established.

8.5 Geriatric Use

Clinical studies of phenylephrine did not include sufficient numbers of subjects aged 65 and over to determine whether they respond differently from younger subjects. Other reported clinical experience has not identified differences in responses between the elderly and younger patients. In general, dose selection for an elderly patient should be cautious, usually starting at the low end of the dosing range, reflecting the greater frequency of decreased hepatic, renal, or cardiac function, and of concomitant disease or other drug therapy.

8.6 Hepatic Impairment

In patients with liver cirrhosis [Child Pugh Class A (n=3), Class B (n=5) and Class C (n=1)], dose-response data indicate decreased responsiveness to phenylephrine. Consider using larger doses than usual in hepatic impaired subjects.

8.7 Renal Impairment

In patients with end stage renal disease (ESRD) undergoing hemodialysis, dose-response data indicates increased responsiveness to phenylephrine. Consider using lower doses of phenylephrine hydrochloride in ESRD patients.

10 OVERDOSAGE

Overdose of IMMPHENTIV 100 mcg/mL and phenylephrine hydrochloride injection 10 mg/mL can cause a rapid rise in blood pressure. Symptoms of overdose include headache, vomiting, hypertension, reflex bradycardia, and cardiac arrhythmias including ventricular extrasystoles and ventricular tachycardia, and may cause a sensation of fullness in the head and tingling of the extremities. Consider using an α-adrenergic antagonist.

11 DESCRIPTION

Phenylephrine Hydrochloride Injection and IMMPHENTIV® injection contain active pharmaceutical ingredient phenylephrine in the form of hydrochloride salt. Phenylephrine is a synthetic sympathomimetic agent in sterile form for parenteral injection. Phenylephrine hydrochloride chemical name is (-)-m-Hydroxy-α [(methylamino)methyl]benzyl alcohol hydrochloride and has the following structural formula:

Phenylephrine hydrochloride is very soluble in water, freely soluble in ethanol, and insoluble in chloroform and ethyl ether. Phenylephrine hydrochloride is sensitive to light.

IMMPHENTIV® Injection, 100 mcg/mL:

IMMPHENTIV®, USP, is a clear, colorless, aqueous solution that is essentially free of visible foreign matter, and Ready-To-Use formulation.

Each mL contains: 100 mcg of Phenylephrine Hydrochloride USP (equivalent to 82 mcg of phenylephrine base), 7.5 mg of Sodium Chloride USP as tonicity agent; 4 mg of Sodium Citrate Dihydrate USP, and 1 mg of Citric Acid Monohydrate USP, as buffering agents, 0.2 mg of Edetate Disodium USP as chelating agent, and Sodium Hydroxide NF and Hydrochloric Acid NF as pH adjusters, in Water for Injection USP. IMMPHENTIV® injection pH range is 3.0 to 6.5.

Phenylephrine Hydrochloride Injection, USP, 10 mg/mL:

Phenylephrine Hydrochloride injection, USP is a clear, colorless, aqueous solution that is essentially free of visible foreign matter. It MUST BE DILUTED before administration as bolus intravenous infusion or continuous intravenous infusion.

Each mL contains: 10 mg of Phenylephrine Hydrochloride (equivalent to 8.2 mg of phenylephrine base); 3.5 mg of Sodium Chloride USP as tonicity agent; 1 mg of Citric Acid Monohydrate USP and 4 mg of Sodium Citrate Dihydrate USP, as buffering agents; 2 mg of Sodium Metabisulfite USP, as antioxidant, and Sodium Hydroxide NF and Hydrochloric Acid NF, as pH adjusters in Water for Injection. Phenylephrine Hydrochloride injection pH range is 3.0 to 6.5.

12 CLINICAL PHARMACOLOGY

12.1 Mechanism of Action

Phenylephrine hydrochloride is an α-1 adrenergic receptor agonist.

12.2 Pharmacodynamics

Phenylephrine is the active moiety. Metabolites are inactive at both the α-1and α-2 adrenergic receptors. Following parenteral administration of phenylephrine hydrochloride, increases in systolic blood pressure, diastolic blood pressure, mean arterial blood pressure, and total peripheral vascular resistance are observed. The onset of blood pressure increase following an intravenous bolus phenylephrine hydrochloride administration is rapid and the effect may persist for up to 20 minutes. As mean arterial pressure increases following parenteral doses, vagal activity also increases, resulting in reflex bradycardia.

Most vascular beds are constricted, including renal, splanchnic, and hepatic.

12.3 Pharmacokinetics

Following an intravenous infusion of phenylephrine hydrochloride, the effective half-life was approximately 5 minutes. The steady-state volume of distribution (340 L) exceeded the body volume by a factor of 5, suggesting a high distribution into certain organ compartments. The average total serum clearance (2095 mL/min) was close to one-third of the cardiac output.

A mass balance study showed that phenylephrine is extensively metabolized by the liver with only 12% of the dose excreted unchanged in the urine. Deamination by monoamino oxidase is the primary metabolic pathway resulting in the formation of the major metabolite (m-hydroxymandelic acid) which accounts for 57% of the total administered dose.

13 NONCLINICAL TOXICOLOGY

13.1 Carcinogenesis, Mutagenesis, Impairment of Fertility

Carcinogenesis:

Long-term animal studies that evaluated the carcinogenic potential of orally administered phenylephrine hydrochloride in F344/N rats and B6C3F1 mice were completed by the National Toxicology Program using the dietary route of administration. There was no evidence of carcinogenicity in mice administered approximately 270 mg/kg/day (131-times the human daily dose (HDD) of 10 mg/day based on body surface area) or rats administered approximately 50 mg/kg/day (48-times the HDD based on body surface area comparisons).

Mutagenesis:

Phenylephrine hydrochloride tested negative in the in vitro bacterial reverse mutation assay (S. typhimurium strains TA98, TA100, TA1535 and TA1537), the in vitro chromosomal aberrations assay, the in vitro sister chromatid exchange assay, and the in vivo rat micronucleus assay. Positive results were reported in only one of two replicates of the in vitro mouse lymphoma assay.

Impairment of Fertility:

No adverse effects on fertility or early embryonic development were noted when phenylephrine hydrochloride was administered at doses of 50 mcg, 100 mcg, or 200 mcg/kg/day (up to 0.2 times HDD of 10 mg/60 kg/day based on body surface area) via single daily bolus injection for 28 days prior to mating to male rats or for 14 days prior to mating through Gestation Day 7 to female rats.

14 CLINICAL STUDIES

Increases in systolic and mean blood pressure following administration of phenylephrine were observed in 42 literature-based studies in the perioperative setting, including 26 studies where phenylephrine was used in low-risk (ASA 1 and 2) pregnant women undergoing neuraxial anesthesia during cesarean delivery, 3 studies in non-obstetric surgery under neuraxial anesthesia, and 13 studies in patients undergoing surgery under general anesthesia. Mean arterial blood pressure increases were also observed in two double-blind, active-controlled studies in patients with septic shock.

16 HOW SUPPLIED/STORAGE AND HANDLING

IMMPHENTIV® injection, USP, 100 mcg/mL Ready-to-Use vials is supplied as follows:

- NDC 0641-6245-10: 500 mcg in 5 mL (100 mcg/mL) single-dose vials packaged in cartons containing 10 vials per carton
- NDC 0641-6246-10: 1,000 mcg in 10 mL (100 mcg/mL) single-dose vials packaged in cartons containing 10 vials per carton

Store at 20°C to 25°C (68°F to 77°F), excursions permitted to 15°C to 30°C (59°F to 86°F) [see USP Controlled Room Temperature]. Protect from light. Discard any unused portion.

Phenylephrine Hydrochloride injection, USP, 10 mg/mL, is supplied as follows:

- NDC 0641-6142-25: 10 mg in 1 mL fill (10 mg/mL) in 2 mL single-dose vials packaged in cartons containing 25 vials per carton
- NDC 0641-6188-10: 50 mg in 5 mL (10 mg/mL) Pharmacy Bulk Package vials packed in cartons containing 10 vials per carton
- NDC 0641-6189-10: 100 mg in 10 mL (10 mg/mL) Pharmacy Bulk Package vials packed in cartons containing 10 vials per carton

Store at 20°C to 25°C (68°F to 77°F), excursions permitted to 15°C to 30°C (59°F to 86°F) [See USP Controlled Room Temperature]. Protect from light. Keep covered in carton until time of use.

The 1 mL vials are for single-dose only. Discard any unused portion.

The 5 mL and 10 mL vials are pharmacy bulk packages. The diluted solution should not be held for more than 4 hours at room temperature or for more than 24 hours under refrigerated conditions (2°C – 8°C). Discard any unused portion.

17 PATIENT COUNSELING INFORMATION

Inform patients, families, or caregivers that the primary side effect of phenylephrine is hypertension and, rarely, hypertensive crisis. Patients may experience bradycardia (slow heart rate), which in some cases may produce heart block or other cardiac arrhythmias, extra ventricular beats, myocardial ischemia in patients with underlying cardiac disease, and pulmonary edema (fluid in the lungs) or rales. Common, less serious symptoms include the following:

- chest pain
- skin or tissue damage if the drug leaks out of the venous catheter into the surrounding tissue
- headache, nervousness, tremor, numbness/tingling (paresthesias) in hands or feet
- nausea, vomiting
- excitability, dizziness, sweating, flushing

Manufactured by:

Hikma Pharmaceuticals USA Inc.

Berkeley Heights, NJ 07922

Revised: March 2023

462-664-05

PRINCIPAL DISPLAY PANEL

NDC 0641-6142-01
Phenylephrine
HCl Injection, USP
10 mg/mL
For Intravenous
Use
Dilute before use
Protect from light
1 mL Single Dose Vial

NDC 0641-6142-25 Rx only
Phenylephrine
HCl Injection, USP
10 mg/mL
For Intravenous Use
Dilute before use
25 x 1 mL Single Dose Vials
Discard unused portion

PRINCIPAL DISPLAY PANEL

NDC 0641-6188-01 Rx only
Phenylephrine
HCl Injection, USP
50 mg/5 mL (10 mg/mL)
Pharmacy Bulk Package
Not for Direct Infusion
For Intravenous Use
Must Be Diluted
Protect From Light 5 mL Vial

NDC 0641-6188-10 Rx only
Phenylephrine
HCl Injection, USP
50 mg/5 mL (10 mg/mL)
Pharmacy Bulk Package
Not for Direct Infusion
For Intravenous Use
Must Be Diluted - Protect From Light
Store in carton until time of use
10 x 5 mL Vials

PRINCIPAL DISPLAY PANEL

NDC 0641-6189-01 Rx only
Phenylephrine
HCl Injection, USP
100 mg/10 mL (10 mg/mL)
Pharmacy Bulk Package
Not for Direct Infusion
For Intravenous Use
Must Be Diluted
Protect From Light
10 mL Vial

NDC 0641-6189-10 Rx only
Phenylephrine
HCl Injection, USP
100 mg/10 mL (10 mg/mL)
Pharmacy Bulk Package
Not for Direct Infusion
For Intravenous Use
Must Be Diluted - Protect From Light
Store in carton until time of use
10 x 10 mL vials

PRINCIPAL DISPLAY PANEL

NDC 0641-6245-01 Rx only

IMMPHENTIV

Phenylephrine HCl Injection, USP

500 mcg per 5 mL (100 mcg/mL)

For Intravenous Use

Ready to Use - Do NOT Dilute

NDC 0641-6245-10 Rx only

IMMPHENTIV

Phenylephrine HCl Injection, USP

500 mcg per 5 mL (100 mcg/mL)

For Intravenous Use

Ready to Use - Do NOT Dilute

10 x 5 mL Single-Dose Vials

PRINCIPAL DISPLAY PANEL

NDC 0641-6246-01 Rx only

IMMPHENTIV

Phenylephrine HCl Injection, USP

1,000 mcg per 10 mL (100 mcg/mL)

For Intravenous Use

Ready to Use - Do NOT Dilute

NDC 0641-6246-10 Rx only

IMMPHENTIV

Phenylephrine HCl Injection, USP

1,000 mcg per 10 mL (100 mcg/mL)

For Intravenous Use

Ready to Use - Do NOT Dilute

10 x 10 mL Single-Dose Vials